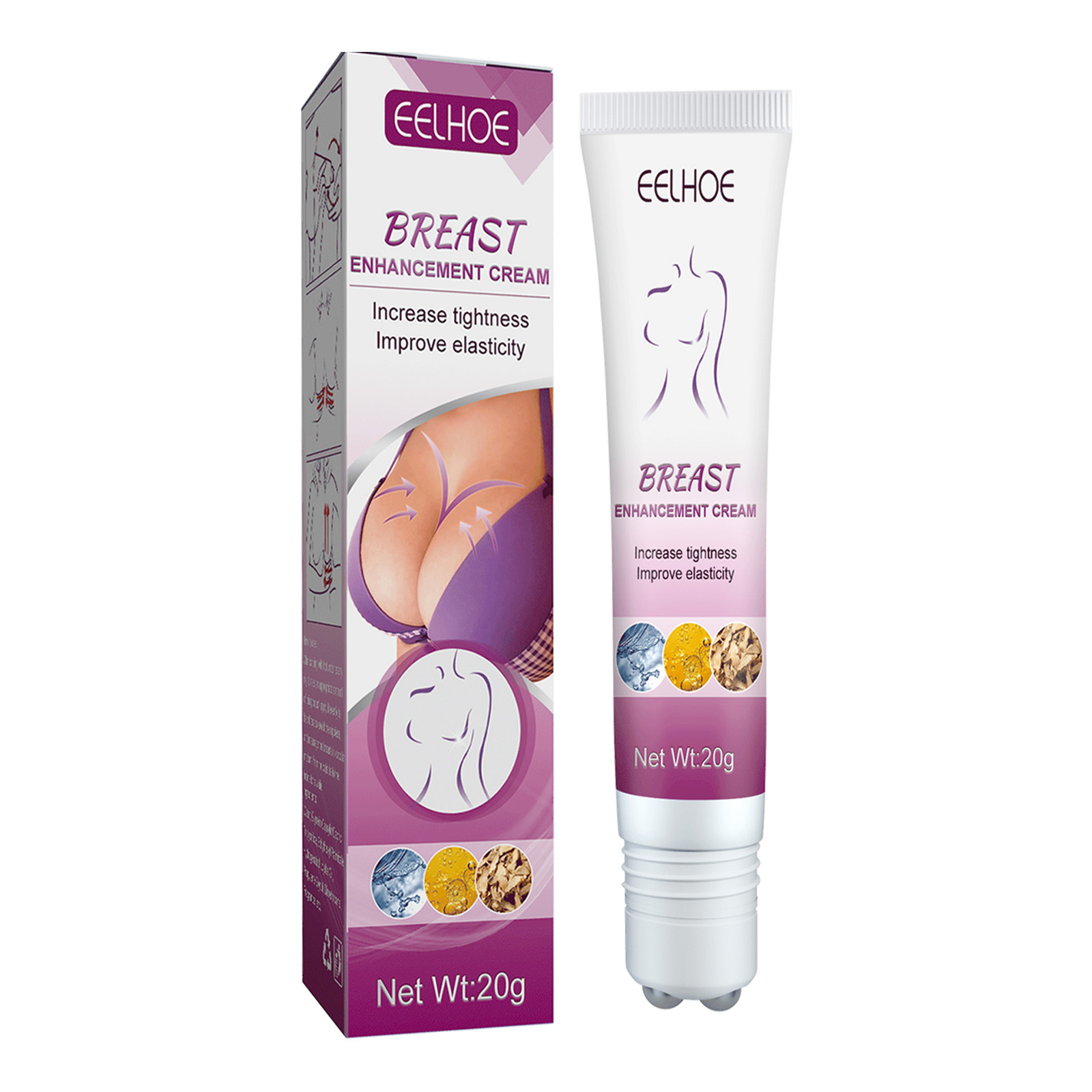 DRUG LABEL: Breast Enhancement Cream
NDC: 83675-017 | Form: CREAM
Manufacturer: Guangzhou Hanhai Trading Co., Ltd
Category: otc | Type: HUMAN OTC DRUG LABEL
Date: 20231007

ACTIVE INGREDIENTS: GLYCERIN 18 g/100 g
INACTIVE INGREDIENTS: COPTIS TEETA ROOT; WATER

Active Ingredient

Glycerin 18.0%

Purpose

Slimming

Use

Increase tightness
Improve elasticity

Warnings

For external use only. Do not take it internally.

Keep Out Of Reach Of Children
Sensitive Skin

Do not use

Product shall not be eat

When Using

1.Take an approprlateamount of product and put it back in the palm of your hand.
2.Gently massage 5 times around the chest and glide to the neck in acircular motion.
3.support your breasts with your palms and push up slightly.
4.Put your hands on your breastbone and massage gently towards your underarms.

Stop Use

In case of adverse reactions, please stop using this product.If the symptoms.

Ask Doctor

ask doctor in case of Sensitive Skin

Keep Oot Of Reach Of Children

Keep Out Of Reach Of Children

Directions

1.Take an approprlateamount of product and put it back in the palm of your hand.
2.Gently massage 5 times around the chest and glide to the neck in acircular motion.
3.support your breasts with your palms and push up slightly.
4.Put your hands on your breastbone and massage gently towards your underarms.

Other information

Store the product in a cool, dry and well-ventilated place

Avoid direct sunlight

Inactive ingredients

Rhizoma

Water